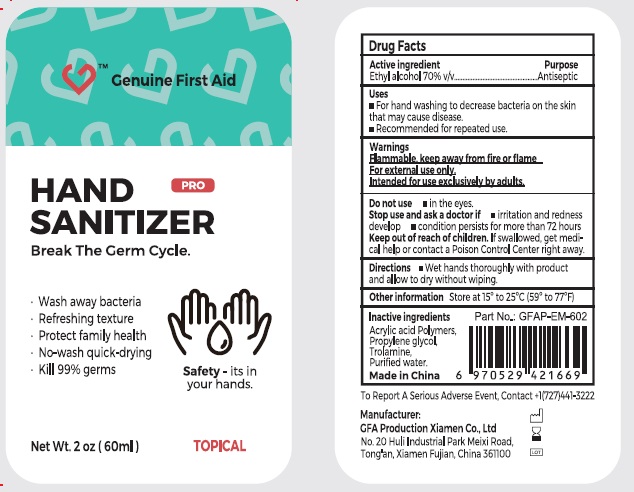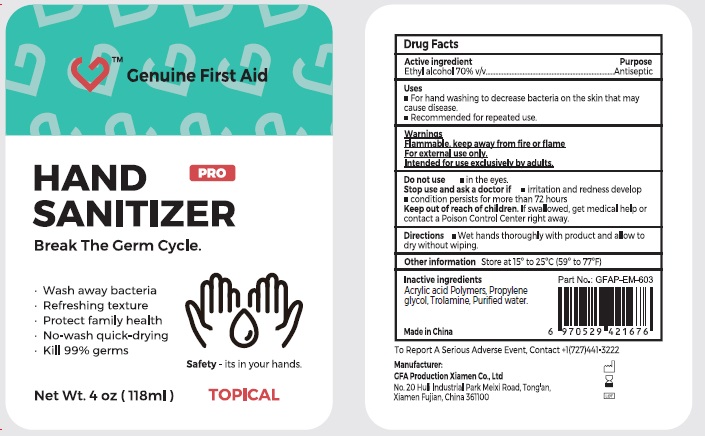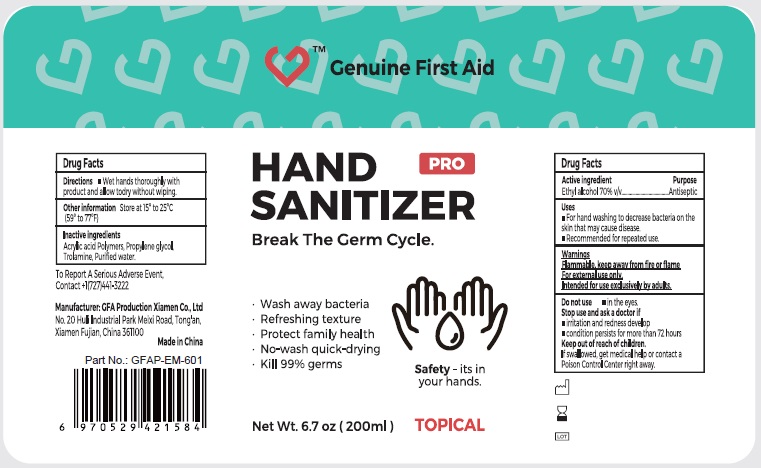 DRUG LABEL: Genuine First Aid Hand Sanitizer Ethyl Alcohol
NDC: 50814-060 | Form: GEL
Manufacturer: GFA Production (Xiamen) Co., Ltd.
Category: otc | Type: HUMAN OTC DRUG LABEL
Date: 20241015

ACTIVE INGREDIENTS: ALCOHOL 0.7 mL/1 mL
INACTIVE INGREDIENTS: PROPYLENE GLYCOL; TROLAMINE; WATER

Genuine First Aid Hand Sanitizer Ethyl Alcohol

Active ingredient

Ethyl alcohol 70% v/v

Purpose

Antiseptic

Uses

- For hand washing to decrease bacteria on the skin that may cause disease.
- Recommended for repeated use.

Warnings

Flammable, keep away from fire or flame

For external use only.

Intended for use exclusively by adults.

Do not use

- in the eyes.

Stop use and ask a doctor if

- irritation and redness develop
- condition persists for more than 72 hours

Keep out of reach of children.

If swallowed, get medical help or contact a Poison Control Center right away.

Directions

- Wet hands thoroughly with product and allow to dry without wiping.

Other information

Store at 15° to 25°C (59° to 77°F)

Inactive ingredients

Acrylic acid Polymers, Propylene glycol, Trolamine, Purified water.